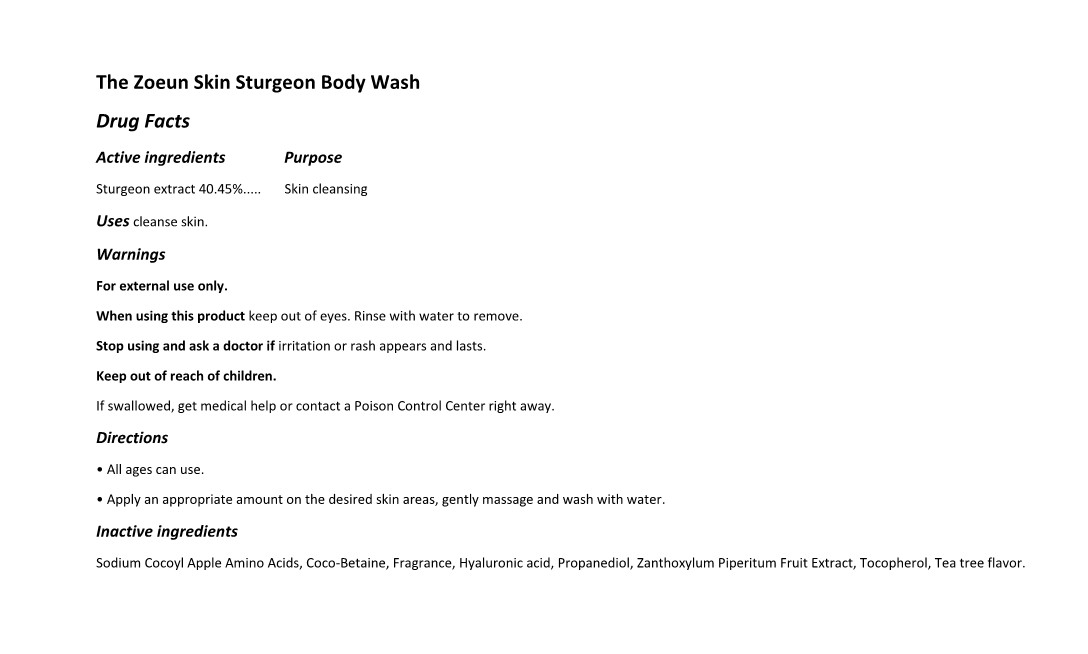 DRUG LABEL: The Zoeun Skin Sturgeon Body Wash
NDC: 83636-606 | Form: SOLUTION
Manufacturer: Sturgeonbio Co.,Ltd.
Category: otc | Type: HUMAN OTC DRUG LABEL
Date: 20240101

ACTIVE INGREDIENTS: STURGEON, UNSPECIFIED 40.45 g/100 mL
INACTIVE INGREDIENTS: HYALURONIC ACID; SODIUM COCOYL APPLE AMINO ACIDS; ZANTHOXYLUM PIPERITUM FRUIT PULP; COCAMIDOPROPYL BETAINE; TOCOPHEROL; FRAGRANCE 13576; PROPANEDIOL; MELALEUCA ALTERNIFOLIA (TEA TREE) LEAF OIL

83636-606 The Zoeun Skin Sturgeon Body Wash

Active Ingredients

Sturgeon extract 40.45%

Purposes

Skin cleansing

Uses

cleanse skin

Warnings

Keep out of reach of children.
If swallowed, get medical help or contact a Poison Control Center right away.

Warnings

Stop using and ask a doctor if irritation or rash appears and lasts.

Warnings

When using this product keep out of eyes. Rinse with water to remove

Warnings

For external use only.

Directions

• All ages can use.
• Apply an appropriate amount on the desired skin areas, gently massage and wash with water.

Inactive Ingredients

Sodium Cocoyl Apple Amino Acids, Coco-Betaine, Fragrance, Hyaluronic acid, Propanediol, Zanthoxylum Piperitum Fruit Extract, Tocopherol, Tea tree flavor